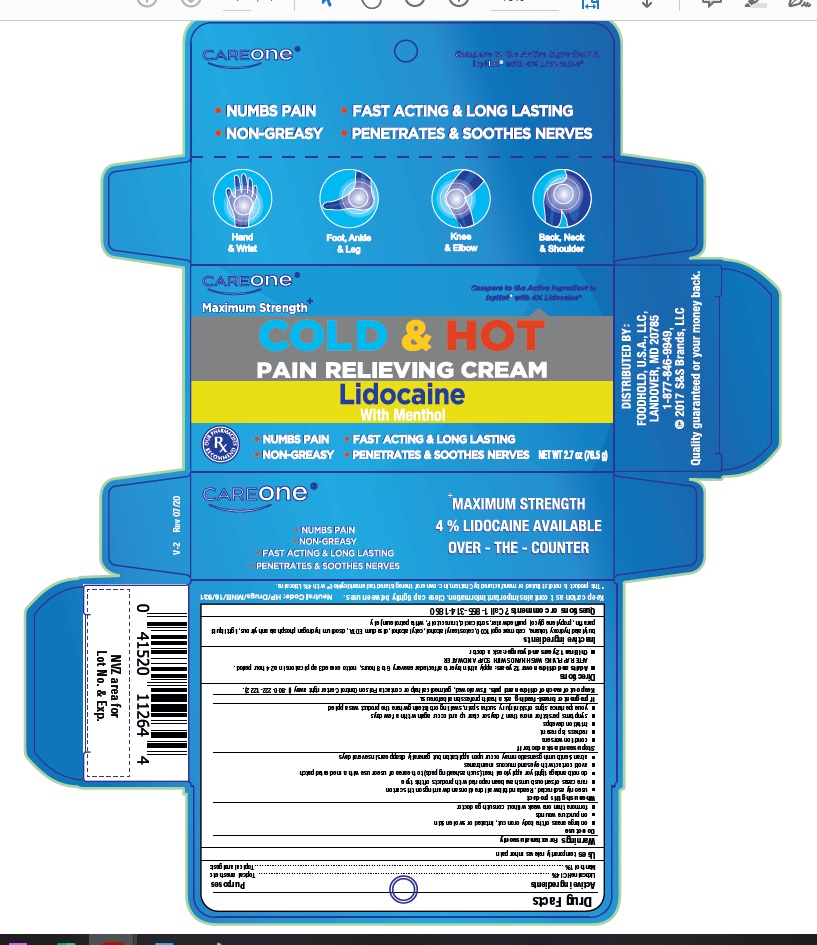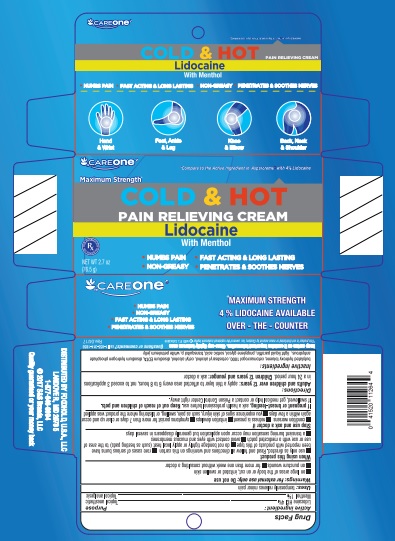 DRUG LABEL: Hot and Cold Cream with Lidocaine- RA

NDC: 76168-200 | Form: CREAM
Manufacturer: Velocity Pharma LLC
Category: otc | Type: HUMAN OTC DRUG LABEL
Date: 20221120

ACTIVE INGREDIENTS: LIDOCAINE 0.4 g/1 g; MENTHOL 0.1 g/1 g
INACTIVE INGREDIENTS: BUTYLATED HYDROXYTOLUENE; CETOSTEARYL ALCOHOL; CETETH-2; CETYL ALCOHOL; EDETATE DISODIUM; SODIUM PHOSPHATE, DIBASIC, ANHYDROUS; LIGHT MINERAL OIL; PROPYLENE GLYCOL; SORBIC ACID; PETROLATUM

Hot and Cold Pain Relieving Cream with Lidocaine- Careone

Drug Facts

HOT AND COLD CREAM with LIDOCAINE- RA

PAIN RELIEVING CREAM

Drug Facts

Active Ingredients

Lidocaine HCl 4%

Menthol 1%

Purposes

Lidocaine- Topical anesthetic,

Menthol- Topical Analgesic

Uses

Temporarily relieves minor pain

Warnings

For external use only

Do not use

- on large areas of the body or on cut, irritated or swollen skin
- on puncture wounds
- for more than one week without consulting a doctor

When using this product

- Use only as directed. Read and follow all directions and warnings on this label
- rare cases of serious burns have been reported with products of this type
- do not bandage tightly or apply local heat (such as heating pads) to the area of use or use with a medicated patch
- avoid contact with eyes and mucous membranes
- a transient burning sensation may occur upon application but generally disappears in several days

Stop use and ask a doctor if

- condition worsens
- redness is present
- irritation develops
- symptoms persist for more than 7 days or clear up and occur again within a few days
- you experience signs of skin injury, such as pain, swelling, or blistering where the product was applied

If pregnant or breast-feeding,

ask a health professional before use.

Keep out of reach of children and pets.

If swallowed, get medical help or contact a Poison Control Center right away.

Directions

adults and children over 12 years:

- apply a thin layer to affected area every 6 to 8 hours, not to exceed 3 applications in a 24 hour period
- AFTER APPLYING, WASH HANDS WITH SOAP AND WATER

children 12 years or younger: ask a doctor

Inactive ingredients

Butylated hydroxyl toluene,cetostearyl alcohol,cetomacrogol 1000,cetyl alcohol,disodium EDTA,disodium hydrogen phosphate,light liquid paraffin,propylene glycol,sorbic acid,transquitol P, white petroleum jelly

Keep Carton As It Contains Important Information

Close cap tightly between uses.

PRINCIPAL DISPLAY PANEL

Hot and cold Cream -CareOne
Net Wt 2.7 OZ (76.5 g)